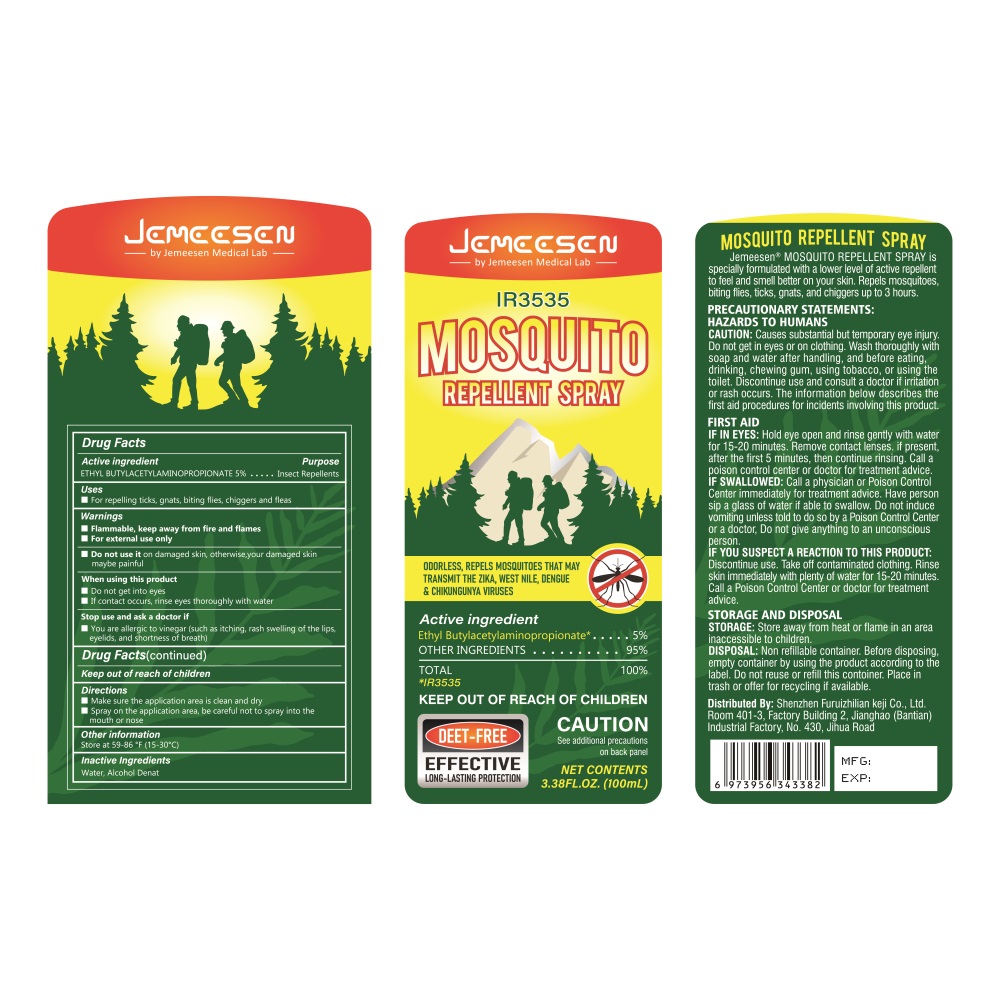 DRUG LABEL: MOSQUITO REPELLENT
NDC: 84445-003 | Form: LIQUID
Manufacturer: Shenzhen Furuizhilian keji Co., Ltd.
Category: otc | Type: HUMAN OTC DRUG LABEL
Date: 20240711

ACTIVE INGREDIENTS: ETHYL BUTYLACETYLAMINOPROPIONATE 5 g/100 mL
INACTIVE INGREDIENTS: ALCOHOL; WATER

MOSQUITO REPELLENT SPRAY

Active inpradients

ETHYL BUTYLACETYLAMINOPROPIONATE 5%

Purpose

Insect Repellents

Uses

Make sure the application area is clean and dry.
Spray on the application area, be careful not to spray into the mouth or nose

Warings

Flammable, keep away from fire and flames.
For external use only

Do not use

on damaged skin

When using this product

Do not get into eyes.
If contact occurs, rinse eyes thoroughly with water.

Stop use and ask a doctor if

irritation and redness develop. If condition persists more than 48 hours.

Keep out of reach of children

If swallowed, get medical help or contact a Poison Control Center right away.

DOSAGE AND ADMINISTRATION

Use when going out or when there are many mosquitoes
Test on a small area before first use, and continue to use if there is no discomfort after 24 hours
Spray the area 2-3 times when using

INACTIVE INGREDIENT

Water, Alcohol Denat